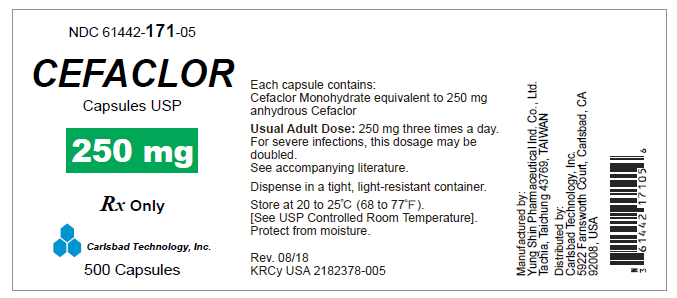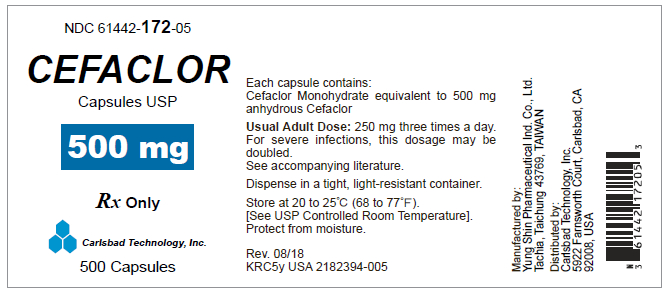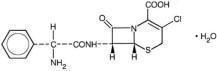 DRUG LABEL: Cefaclor
NDC: 61442-171 | Form: CAPSULE
Manufacturer: Carlsbad Technology, Inc.
Category: prescription | Type: HUMAN PRESCRIPTION DRUG LABEL
Date: 20250501

ACTIVE INGREDIENTS: CEFACLOR 250 mg/1 1
INACTIVE INGREDIENTS: MAGNESIUM STEARATE; SODIUM STARCH GLYCOLATE TYPE A POTATO; LACTOSE MONOHYDRATE; TALC; GELATIN; TITANIUM DIOXIDE; FD&C BLUE NO. 1; FD&C RED NO. 3; SHELLAC; AMMONIA; POTASSIUM HYDROXIDE; FERROSOFERRIC OXIDE; ALCOHOL; ISOPROPYL ALCOHOL; TERT-BUTYL ALCOHOL; PROPYLENE GLYCOL

Cefaclor Capsules USP

Rx Only

To reduce the development of drug-resistant bacteria and maintain the effectiveness of Cefaclor Capsule and other antibacterial drugs, Cefaclor Capsules USP should be used only to treat or prevent infections that are proven or strongly suspected to be caused by bacteria.

DESCRIPTION

Cefaclor, USP is a semisynthetic cephalosporin antibiotic for oral administration. It is chemically designated as 3-chloro-7-D-(2-phenylglycinamido)-3-cephem-4-carboxylic acid monohydrate. The chemical formula for cefaclor is C15H14ClN3O4S • H2O and the molecular weight is 385.82.

Each 250-mg capsule contains cefaclor monohydrate equivalent to 250 mg (0.68 mmol) of anhydrous cefaclor and inactive ingredients: magnesium stearate, sodium starch glycolate, lactose monohydrate, talc. The 250 mg capsule shell contains gelatin, titanium dioxide, FD & C Blue No. 1, FD & C Red No. 3, and imprinting ink components: shellac, strong ammonia solution, potassium hydroxide, black iron oxide, .dehydrated alcohol, isopropyl alcohol, butyl alcohol and propylene glycol.

Each 500-mg capsule contains cefaclor monohydrate equivalent to 500 mg (1.36 mmol) of anhydrous cefaclor and inactive ingredients: magnesium stearate, sodium starch glycolate, lactose monohydrate, talc. The 500 mg capsule shell contains gelatin, titanium dioxide, FD & C Blue No. 1, FD & C Red No. 3, FD & C Yellow No. 6, FD & C Red No. 40, and imprinting ink components: shellac, strong ammonia solution, titanium dioxide, FD & C Blue No. 1 aluminum lake, dehydrated alcohol, isopropyl alcohol, butyl alcohol and propylene glycol.

CLINICAL PHARMACOLOGY

Cefaclor is well absorbed after oral administration to fasting subjects. Total absorption is the same whether the drug is given with or without food; however, when it is taken with food, the peak concentration achieved is 50% to 75% of that observed when the drug is administered to fasting subjects and generally appears from three fourths to 1 hour later. Following administration of 250-mg, 500-mg, and 1-g doses to fasting subjects, average peak serum levels of approximately 7, 13, and 23 mcg/mL respectively were obtained within 30 to 60 minutes. Approximately 60% to 85% of the drug is excreted unchanged in the urine within 8 hours, the greater portion being excreted within the first 2 hours. During this 8-hour period, peak urine concentrations following the 250-mg, 500-mg and 1-g doses were approximately 600, 900 and 1,900 mc g/mL, respectively. The serum half-life in normal subjects is 0.6 to 0.9 hour. In patients with reduced renal function, the serum half-life of cefaclor is slightly prolonged. In those with complete absence of renal function, the plasma half-life of the intact molecule is 2.3 to 2.8 hours. Excretion pathways in patients with markedly impaired renal function have not been determined. Hemodialysis shortens the half-life by 25% to 30%.

Microbiology

Mechanism of Action
As with other cephalosporins, the bactericidal action of cefaclor results from inhibition of cell-wall synthesis.

Mechanism of Resistance

Resistance to cefaclor is primarily through hydrolysis of beta-lactamases, alteration of penicillin-binding proteins (PBPs) and decreased permeability. Pseudomonasspp ., Acinetobacter calcoaceticus and most strains of Enterococi (Enterococcus faecalis,group D streptococci), Enterobacter spp .,indole-positive Proteus, Morganella morganii (formerly Proteus morganii), Providencia rettgeri (formerly Proteus rettgeri) and Serratia spp. are resistant to cefaclor. Cefaclor is inactive against methicillin-resistant staphylococci. β-lactamase-negative, ampicillin-resistant strains of H. influenzae should be considered resistant to cefaclor despite apparent in vitro susceptibility to this agent.

Antibacterial Activity
Cefaclor has been shown to be active against most strains of the following microorganisms both in vitro and in clinical infections as described in the INDICATIONS AND USAGE section.

Gram-positive Bacteria
Staphylococcus aureus (methicillin susceptible only)
Coagulase negative staphylococci (methicillin susceptible only)
Streptococcus pneumoniae
Streptococcus pyogenes (group A β-hemolytic streptococci)

Gram-negative Bacteria
Escherichia coli
Haemophilus influenzae (excluding β-lactamase-negative, ampicillin-resistant strains)
Klebsiella spp.
Proteus mirabilis

The following in vitro data are available, but their clinical significance is unknown. At least 90 percent of the following bacteria exhibit an in vitro minimum inhibitory concentrations (MICs) less than or equal to the susceptible breakpoint of cefaclor. However, the safety and effectiveness of cefaclor in treating clinical infections due to these bacteria has not been established in adequate and well-controlled trials.

Gram-negative Bacteria
Citrobacter diversus
Moraxella catarrhalis
Neisseria gonorrhoeae

Anaerobic Bacteria
Bacteroides spp.
Peptococcus spp.
Peptostreptococcus spp.
Propionibacterium acnes

Susceptibility Testing
For specific information regarding susceptibility test interpretive criteria and associated test methods and quality control standards recognized by FDA for this drug, please see: https://www.fda.gov/STIC.

INDICATIONS AND USAGE

Cefaclor is indicated in the treatment of the following infections when caused by susceptible strains of the designated microorganisms:

Otitis media caused by Streptococcus pneumoniae, Haemophilus influenzae,staphylococci, and Streptococcus pyogenes

Note: β-lactamase-negative, ampicillin-resistant (BLNAR) strains of Haemophilus influenzae should be considered resistant to cefaclor despite apparent in vitro susceptibility of some BLNAR strains.

Lower respiratory tract infections, including pneumonia, caused by Streptococcus pneumoniae, Haemophilus influenzae,and Streptococcus pyogenes

Note: β-lactamase-negative, ampicillin-resistant (BLNAR) strains of Haemophilus influenzae should be considered resistant to cefaclor despite apparent in vitro susceptibility of some BLNAR strains.

Pharyngitis and Tonsillitis, caused by Streptococcus pyogenes

Note:Penicillin is the usual drug of choice in the treatment and prevention of streptococcal infections, including the prophylaxis of rheumatic fever. Cefaclor is generally effective in the eradication of streptococci from the nasopharynx; however, substantial data establishing the efficacy of cefaclor in the subsequent prevention of rheumatic fever are not available at present.

Urinary tract infections, including pyelonephritis and cystitis, caused by Escherichia coli, Proteus mirabilis, Klebsiella spp .,and coagulase-negative staphylococci

Skin and skin structure infections caused by Staphylococcus aureus and Streptococcus pyogenes

Appropriate culture and susceptibility studies should be performed to determine susceptibility of the causative organism to cefaclor.

To reduce the development of drug-resistant bacteria and maintain the effectiveness of Cefaclor Capsule and other antibacterial drugs, Cefaclor Capsule should be used only to treat or prevent infections that are proven or strongly suspected to be caused by susceptible bacteria. When culture and susceptibility information are available, they should be considered in selecting or modifying antibacterial therapy. In the absence of such data, local epidemiology and susceptibility patterns may contribute to the empiric selection of therapy.

CONTRAINDICATION

Cefaclor is contraindicated in patients with known allergy to the cephalosporin group of antibiotics.

WARNINGS

BEFORE THERAPY WITH CEFACLOR IS INSTITUTED, CAREFUL INQUIRY SHOULD BE MADE TO DETERMINE WHETHER THE PATIENT HAS HAD PREVIOUS HYPERSENSITIVITY REACTIONS TO CEFACLOR, CEPHALOSPORINS, PENICILLINS, OR OTHER DRUGS. IF THIS PRODUCT IS TO BE GIVEN TO PENICILLIN SENSITIVE PATIENTS, CAUTION SHOULD BE EXERCISED BECAUSE CROSS-HYPERSENSITIVITY AMONG β-LACTAM ANTIBIOTICS HAS BEEN CLEARLY DOCUMENTED AND MAY OCCUR IN UP TO 10% OF PATIENTS WITH A HISTORY OF PENICILLIN ALLERGY.

IF AN ALLERGIC REACTION TO CEFACLOR OCCURS, DISCONTINUE THE DRUG. SERIOUS ACUTE HYPERSENSITIVITY REACTIONS MAY REQUIRE TREATMENT WITH EPINEPHRINE AND OTHER EMERGENCY MEASURES, INCLUDING OXYGEN, INTRAVENOUS FLUIDS, INTRAVENOUS ANTIHISTAMINES, CORTICOSTEROIDS, PRESSOR AMINES, AND AIRWAY MANAGEMENT, AS CLINICALLY INDICATED.

Antibiotics, including cefaclor, should be administered cautiously to any patient who has demonstrated some form of allergy, particularly to drugs.

Pseudomembranous colitis has been reported with nearly all antibacterial agents, including cefaclor, and has ranged in severity from mild to life-threatening. Therefore, it is important to consider this diagnosis in patients who present with diarrhea subsequent to the administration of antibacterial agents.

Treatment with antibacterial agents alters the normal flora of the colon and may permit overgrowth of clostridia. Studies indicate that a toxin produced by Clostridium difficile is one primary cause of antibiotic-associated colitis.

After the diagnosis of pseudomembranous colitis has been established, therapeutic measures should be initiated. Mild cases of pseudomembranous colitis usually respond to drug discontinuation alone. In moderate to severe cases, consideration should be given to management with fluids and electrolytes, protein supplementation and treatment with an antibacterial drug effective against C. difficile.

PRECAUTIONS

General

Prescribing cefaclor in the absence of a proven or strongly suspected bacterial infection or a prophylactic indication is unlikely to provide benefit to the patient and increases the risk of the development of drug-resistant bacteria.

Prolonged use of cefaclor may result in the overgrowth of nonsusceptible organisms. Careful observation of the patient is essential. If superinfection occurs during therapy, appropriate measures should be taken.

Positive direct Coombs' tests have been reported during treatment with the cephalosporin antibiotics. It should be recognized that a positive Coombs' test may be due to the drug, e.g., in hematologic studies or in transfusion cross-matching procedures when antiglobulin tests are performed on the minor side or in Coombs' testing of newborns whose mothers have received cephalosporin antibiotics before parturition.

Cefaclor should be administered with caution in the presence of markedly impaired renal function. Since the half-life of cefaclor in anuria is 2.3 to 2.8 hours, dosage adjustments for patients with moderate or severe renal impairment are usually not required. Clinical experience with cefaclor under such conditions is limited; therefore, careful clinical observation and laboratory studies should be made.

As with other β-lactam antibiotics, the renal excretion of cefaclor is inhibited by probenecid.

Antibiotics, including cephalosporins, should be prescribed with caution in individuals with a history of gastrointestinal disease, particularly colitis.

Information for Patients

Patients should be counseled that antibacterial drugs including cefaclor should only be used to treat bacterial infections. They do not treat viral infections (e.g., the common cold). When cefaclor is prescribed to treat a bacterial infection, patients should be told that although it is common to feel better early in the course of therapy, the medication should be taken exactly as directed. Skipping doses or not completing the full course of therapy may (1) decrease the effectiveness of the immediate treatment and (2) increase the likelihood that bacteria will develop resistance and will not be treatable by cefaclor or other antibacterial drugs in the future.

Drug/Laboratory Test Interactions

Patients receiving cefaclor may show a false-positive reaction for glucose in the urine with tests that use Benedict's and Fehling's solutions and also with Clinitest® tablets.

There have been reports of increased anticoagulant effect when cefaclor and oral anticoagulants were administered concomitantly.

Carcinogenesis, Mutagenesis, Impairment of Fertility

Studies have not been performed to determine potential for carcinogenicity, mutagenicity, or impairment of fertility.

Pregnancy ─ Teratogenic Effects ─ Pregnancy Category B

Reproduction studies have been performed in mice and rats at doses up to 12 times the human dose and in ferrets given 3 times the maximum human dose and have revealed no harm to the fetus due to cefaclor. There are, however, no adequate and well-controlled studies in pregnant women. Because animal reproduction studies are not always predictive of human response, this drug should be used during pregnancy only if clearly needed.

Labor and Delivery

The effect of cefaclor on labor and delivery is unknown.

Nursing Mothers

Small amounts of cefaclor have been detected in mother's milk following administration of single 500-mg doses. Average levels were 0.18, 0.20, 0.21, and 0.16 mcg/mL at 2, 3, 4, and 5 hours respectively. Trace amounts were detected at 1 hour. The effect on nursing infants is not known. Caution should be exercised when cefaclor is administered to a nursing woman.

Pediatric Use

Safety and effectiveness of this product for use in infants less than 1 month of age have not been established.

Geriatric Use

Of the 3703 patients in clinical studies of cefaclor, 594 (16.0%) were 65 and older. No overall differences in safety or effectiveness were observed between these subjects and younger subjects. Other reported clinical experience has not identified differences in responses between the elderly and younger patients, but greater sensitivity of some older individuals cannot be ruled out.

This drug is known to be substantially excreted by the kidney (see CLINICAL PHARMACOLOGY), and the risk of toxic reactions to this drug may be greater in patients with impaired renal function. Because elderly patients are more likely to have decreased renal function, care should be taken in dose selection, and it may be useful in monitor renal function (see DOSAGE AND ADMINISTRATION).

ADVERSE REACTIONS

Adverse effects considered to be related to therapy with cefaclor are listed below:

Hypersensitivity reactions have been reported in about 1.5% of patients and include morbilliform eruptions (1 in 100). Pruritus, urticaria, and positive Coombs' tests each occur in less than 1 in 200 patients.

Cases of serum-sickness-like reactions have been reported with the use of cefaclor. These are characterized by findings of erythema multiforme, rashes, and other skin manifestations accompanied by arthritis/arthralgia, with or without fever, and differ from classic serum sickness in that there is infrequently associated lymphadenopathy and proteinuria, no circulating immune complexes, and no evidence to date of sequelae of the reaction. Occasionally, solitary symptoms may occur, but do not represent a serum-sickness-like reaction. While further investigation is ongoing, serum-sickness-like reactions appear to be due to hypersensitivity and more often occur during or following a second (or subsequent) course of therapy with cefaclor. Such reactions have been reported more frequently in pediatric patients than in adults with an overall occurrence ranging from 1 in 200 (0.5%) in one focused trial to 2 in 8,346 (0.024%) in overall clinical trials (with an incidence in pediatric patients in clinical trials of 0.055%) to 1 in 38,000 (0.003%) in spontaneous event reports. Signs and symptoms usually occur a few days after initiation of therapy and subside within a few days after cessation of therapy; occasionally these reactions have resulted in hospitalization, usually of short duration (median hospitalization = 2 to 3 days, based on postmarketing surveillance studies). In those requiring hospitalization, the symptoms have ranged from mild to severe at the time of admission with more of the severe reactions occurring in pediatric patients. Antihistamines and glucocorticoids appear to enhance resolution of the signs and symptoms. No serious sequelae have been reported.

More severe hypersensitivity reactions, including Stevens-Johnson syndrome, toxic epidermal necrolysis, and anaphylaxis have been reported rarely. Anaphylactoid events may be manifested by solitary symptoms, including angioedema, asthenia, edema (including face and limbs), dyspnea, paresthesias, syncope, hypotension, or vasodilatation. Anaphylaxis may be more common in patients with a history of penicillin allergy.

Rarely, hypersensitivity symptoms may persist for several months.

Gastrointestinal symptoms occur in about 2.5% of patients and include diarrhea (1 in 70).

Onset of pseudomembranous colitis symptoms may occur during or after antibiotic treatment. (see WARNINGS). Nausea and vomiting have been reported rarely. As with some penicillins and some other cephalosporins, transient hepatitis and cholestatic jaundice have been reported rarely.

Other effects considered related to therapy included eosinophilia (1 in 50 patients), genital pruritus, moniliasis or vaginitis (about 1 in 50 patients), and, rarely, thrombocytopenia or reversible interstitial nephritis.

Causal Relationship Uncertain –

CNS ─ Rarely, reversible hyperactivity, agitation, nervousness, insomnia, confusion, hypertonia, dizziness, hallucinations, and somnolence have been reported.

Transitory abnormalities in clinical laboratory test results have been reported. Although they were of uncertain etiology, they are listed below to serve as alerting information for the physician.

Hepatic ─ Slight elevations of AST, ALT, or alkaline phosphatase values (1 in 40).

Hematopoietic ─ As has also been reported with other β-lactam antibiotics, transient lymphocytosis, leukopenia, and, rarely, hemolytic anemia, aplastic anemia, agranulocytosis, and reversible neutropenia of possible clinical significance.

There have been rare reports of increased prothrombin time with or without clinical bleeding in patients receiving cefaclor and Coumadin® concomitantly.

Renal ─ Slight elevations in BUN or serum creatinine (less than 1 in 500) or abnormal urinalysis (less than 1 in 200).

Cephalosporin-class Adverse Reactions

In addition to the adverse reactions listed above that have been observed in patients treated with cefaclor, the following adverse reactions and altered laboratory tests have been reported for cephalosporin-class antibiotics: fever, abdominal pain, superinfection, renal dysfunction, toxic nephropathy, hemorrhage, false positive test for urinary glucose, elevated bilirubin, elevated LDH, and pancytopenia.

Several cephalosporins have been implicated in triggering seizures, particularly in patients with renal impairment when the dosage was not reduced. If seizures associated with drug therapy occur, the drug should be discontinued. Anticonvulsant therapy can be given if clinically indicated (see DOSAGE AND ADMINISTRATIONand OVERDOSAGEsections).

OVERDOSAGE

Signs and Symptoms ─ The toxic symptoms following an overdose of cefaclor may include nausea, vomiting, epigastric distress, and diarrhea. The severity of the epigastric distress and the diarrhea are dose related. If other symptoms are present, it is probable that they are secondary to an underlying disease state, an allergic reaction, or the effects of other intoxication.

Treatment-- To obtain up-to-date information about the treatment of overdose, a good resource is your certified Regional Poison Control Center. Telephone numbers of certified poison control centers are listed in the Physicians' Desk Reference (PDR).In managing overdosage, consider the possibility of multiple drug overdoses, interaction among drugs, and unusual drug kinetics in your patient.

Unless 5 times the normal dose of cefaclor has been ingested, gastrointestinal decontamination will not be necessary.

Protect the patient's airway and support ventilation and perfusion. Meticulously monitor and maintain, within acceptable limits, the patient's vital signs, blood gases, serum electrolytes, etc. Absorption of drugs from the gastrointestinal tract may be decreased by giving activated charcoal, which, in many cases, is more effective than emesis or lavage; consider charcoal instead of or in addition to gastric emptying. Repeated doses of charcoal over time may hasten elimination of some drugs that have been absorbed. Safeguard the patient's airway when employing gastric emptying or charcoal.

Forced diuresis, peritoneal dialysis, hemodialysis, or charcoal hemoperfusion have not been established as beneficial for an overdose of cefaclor.

DOSAGE AND ADMINISTRATION

Cefaclor is administered orally.

Adults ─ The usual adult dosage is 250 mg every 8 hours. For more severe infections (such as pneumonia) or those caused by less susceptible organisms, doses may be doubled.

Pediatric Patients ─ The usual recommended daily dosage for pediatric patients is 20 mg/kg/day in divided doses every 8 hours. In more serious infections, otitis media, and infections caused by less susceptible organisms, 40 mg/kg/day are recommended, with a maximum dosage of 1 g/day.

Cefaclor may be administered in the presence of impaired renal function. Under such a condition, the dosage usually is unchanged (see PRECAUTIONS).

In the treatment of β-hemolytic streptococcal infections, a therapeutic dosage of cefaclor should be administered for at least 10 days.

HOW SUPPLIED

Cefaclor Capsule USP 250 mg (blue cap and pink body hard gelatin capsule containing white to slightly yellowish powder imprinted with ”KRC” on both capsule cap and capsule body) contains cefaclor USP (monohydrate) equivalent to 250 mg anhydrous cefaclor.

Bottle of 30 NDC 61442-171-30

Bottle of 100 NDC 61442-171-01

Bottle of 500 NDC 61442-171-05

Cefaclor Capsule USP 500 mg (blue cap and orange body hard gelatin capsule containing white to slightly yellowish powder imprinted with “KRC500” on both capsule cap and capsule body) contains cefaclor USP (monohydrate) equivalent to 500 mg anhydrous cefaclor.

Bottle of 30 NDC 61442-172-30

Bottle of 100 NDC 61442-172-01

Bottle of 500 NDC 61442-172-05

Store at 20 - 25℃ (68 to 77℉) [See USP Controlled Room Temperature].

Manufactured by:
Yung Shin Pharmaceutical Ind. Co., Ltd.
Yung Shin Pharmaceutical Ind. Co., Ltd.
Tachia, Taichung 43769
TAIWAN

Distributed by:
Carlsbad Technology, Inc.
5922 Farnsworth Court,
Carlsbad, CA 92008, USA

Revised: 02/18

PRINCIPAL DISPLAY PANEL – 250mg Bottle Label

NDC 61442-171-05

CEFACLOR

Capsules USP

250 mg

Rx Only

Carlsbad Technology, Inc.

500 Capsules

PRINCIPAL DISPLAY PANEL – 500mg Bottle Label

NDC 61442-172-05

CEFACLOR

Capsules USP

500 mg

Rx Only

Carlsbad Technology, Inc.

500 Capsules